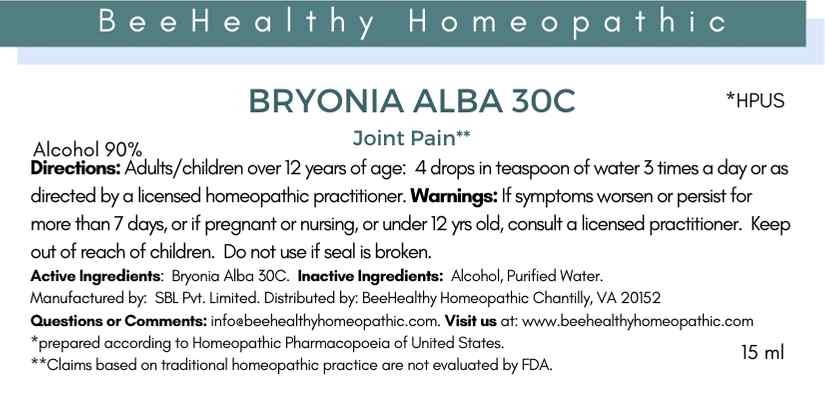 DRUG LABEL: Bryonia Alba
NDC: 79718-1024 | Form: LIQUID
Manufacturer: Warsan Homeopathic
Category: otc | Type: HUMAN OTC DRUG LABEL
Date: 20201110

ACTIVE INGREDIENTS: BRYONIA ALBA ROOT 30 [hp_C]/1 mL
INACTIVE INGREDIENTS: ALCOHOL; WATER

ACTIVE INGREDIENT

Bryonia Alba 30C

INACTIVE INGREDIENT

Alcohol

Purified Water

Stop use and ask doctor if symptoms worsen or persist longer than 7 days.

Do not use if tamper evident seal is missing or broken.

INDICATIONS AND USAGE

Temporary relief from joint pain

PURPOSE

Temporary relief from joint pain

DOSAGE AND ADMINISTRATION

Adults and children 12 years of age and older: Four drops of water in teaspoon of water 3 times a day as needed.

Children under 12 years of age: Consult doctor prior to use.

Keep out of reach of children.